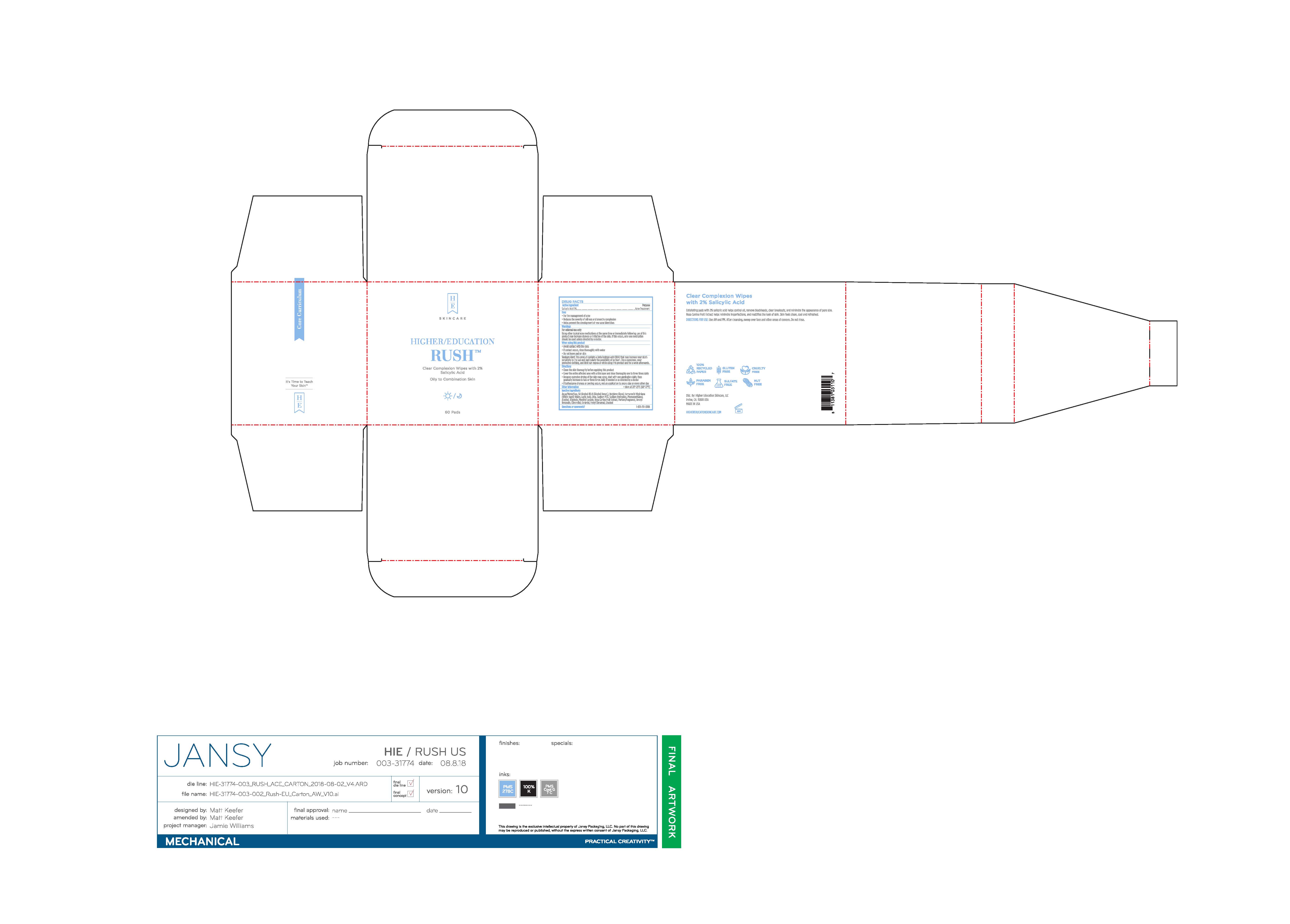 DRUG LABEL: Higher Education Rush Clear Complexion Wipes With 2% Salicylic Acid
NDC: 72936-030 | Form: LIQUID
Manufacturer: Higher Education Skincare, LLC
Category: otc | Type: HUMAN OTC DRUG LABEL
Date: 20221011

ACTIVE INGREDIENTS: SALICYLIC ACID 2 g/100 g
INACTIVE INGREDIENTS: WATER; ALCOHOL; BUTYLENE GLYCOL; HAMAMELIS VIRGINIANA LEAF WATER; LACTIC ACID; UREA; SODIUM HYDRIDE; PHENOXYETHANOL; ALLANTOIN; MENTHYL LACTATE, (-)-; ROSA CANINA FRUIT; BENZYL BENZOATE; CITRONELLAL; GERANIAL; CYCLOHEXYL CINNAMATE; LINALOOL, (+)-

DRUG FACTS

Active Ingredients

Salicylic Acid 0.5%

Purpose

Acne Treatment

Uses

• for the management of acne
• reduces the severity of oiliness and smooths complexion
• helps prevent the development of new acne blemishes

Warnings

For external use only
When using this product
• avoid contact with the eyes
• if contact occurs, rinse thoroughly with water
• using other topical acne medications at the same time or immediately following use of this product may increase dyness or irriation of the skin. If this occurs, only one medication should be used unless directed by a doctor.
• if you develop severe irritation, burning, or itching of the skin

Sunburn Alert: This product contains an alpha hydroxy acid (AHA) that may increase your skin’s sensitivity to the sun and particularly the possibility of sunburn. Use a sunscreen, wear protective clothing, and limit sun exposure while using this product and for a week afterwards.

Keep out of reach of children. If swallowed, get medical help
or contact a Poison Control Center right away.

Directions

• clean the skin thoroughly before applying this product
• cover the entire affected area with a thin layer one to three
times daily
• because excessive drying of the skin may occur, start with
one application daily, then gradually increase to two or three
times daily if needed or as directed by a doctor
• if bothersome dryness or peeling occurs, reduce application
to once a day or every other day

Inactive Ingredients

Aqua/Water/Eau, SD Alcohol 40-B (Alcohol Denat.), Butylene Glycol, Hamamelis Virginiana (Witch Hazel) Water, Lactic Acid, Urea, Sodium PCA, Sodium Hydroxide, Phenoxyethanol, Alcohol, Allantoin, Menthyl Lactate, Rosa Canina Fruit Extract, Parfum/Fragrance, Benzyl Benzoate, Citronellol, Geraniol, Hexyl Cinnamal, Linalool

Other Information

- store at 20-25C (68-77F)

Questions or comments?

1-833-251-0388